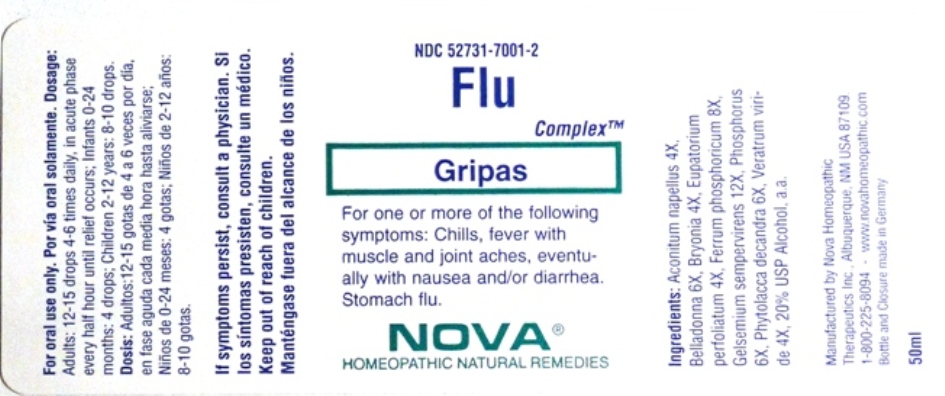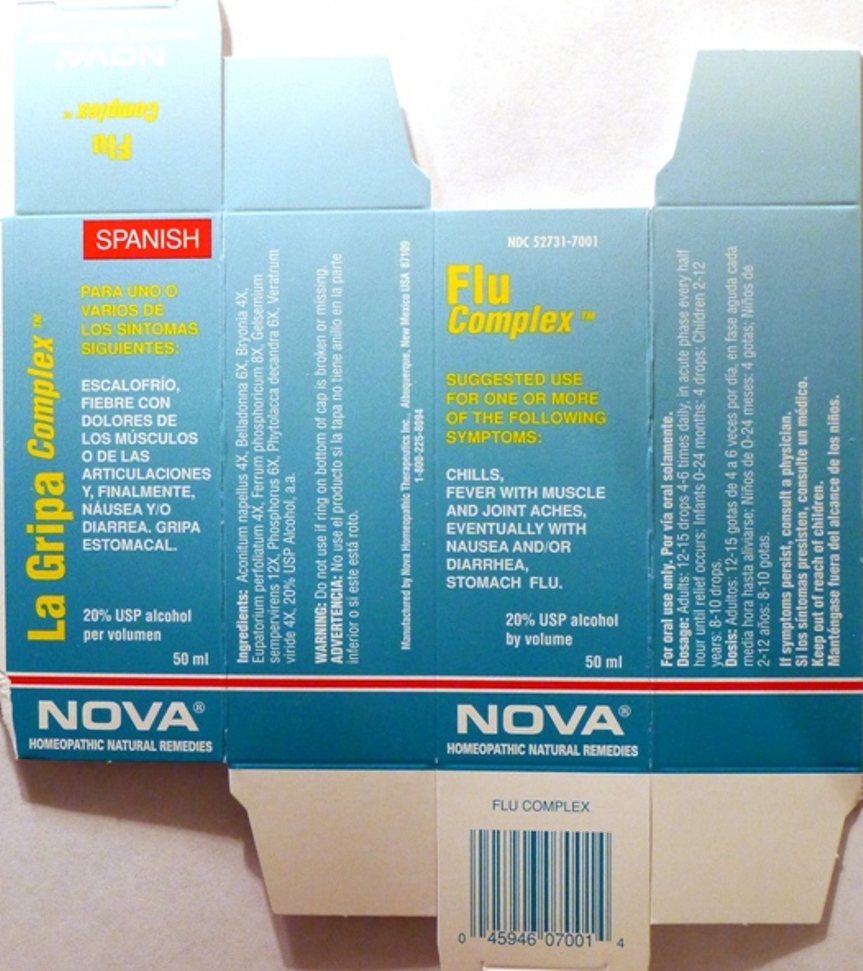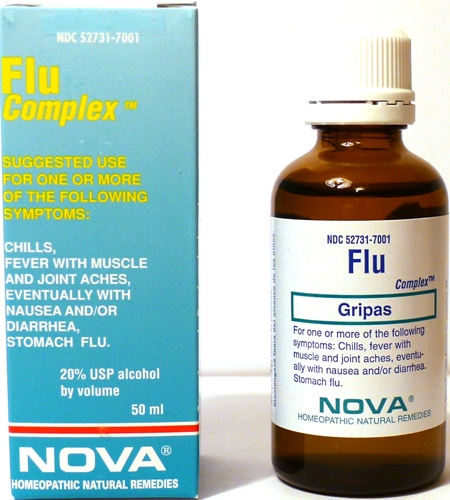 DRUG LABEL: Flu Complex
NDC: 52731-7001 | Form: LIQUID
Manufacturer: Nova Homeopathic Therapeutics, Inc.
Category: homeopathic | Type: HUMAN OTC DRUG LABEL
Date: 20110601

ACTIVE INGREDIENTS: ACONITUM NAPELLUS 4 [hp_X]/1 mL; ATROPA BELLADONNA 6 [hp_X]/1 mL; BRYONIA ALBA ROOT 4 [hp_X]/1 mL; EUPATORIUM PERFOLIATUM FLOWERING TOP 4 [hp_X]/1 mL; FERRUM PHOSPHORICUM 8 [hp_X]/1 mL; GELSEMIUM SEMPERVIRENS ROOT  12 [hp_X]/1 mL; PHOSPHORUS 6 [hp_X]/1 mL; PHYTOLACCA AMERICANA ROOT 6 [hp_X]/1 mL; VERATRUM VIRIDE ROOT 4 [hp_X]/1 mL
INACTIVE INGREDIENTS: ALCOHOL

Flu Complex

Purpose:

Suggested use for one or more of the following symptoms:

Chills, Fever with muscle and joint aches, eventually with nausea and/or diarrhea, stomach flu.

Usage and Dosage:

For oral use only.

DOSAGE AND ADMINISTRATION

Adults:
In Acute Phase:
12-15 drops, every half hour until relief occurs
When Relief Occurs:
12-15 drops, 4-6 times per day
Children 7-12 years:
9 drops, 4-6 times per day

Toddler 2-6 years:

6 drops, 4-6 times daily

Infants 0-24 months:
3 drops, 4-6 times per day

Warnings:

Keep out of reach of children.

WARNINGS

If symptoms persist, consult a physician.
Do not use if ring on bottom of cap is broken or missing.

Active Ingredients:

Aconitum napellus 4X, Belladonna 6X, Bryonia 4X, Eupatorium perfoliatum 4X, Ferrum phosphoricum 8X, Gelsemium
sempervirens 12X, Phosphorus 6X, Phytolacca decandra 6X, Veratrum viride 4X

Inactive Ingredients:

Alcohol, 20% USP

QUESTIONS

Manufactured by Nova Homeopathic Therapeutics Inc., Albuquerque, New Mexico USA 87109
1-800-225-8094

PACKAGE LABEL

Flu Complex Product

Flu Complex Bottle Label

Flu Complex Box